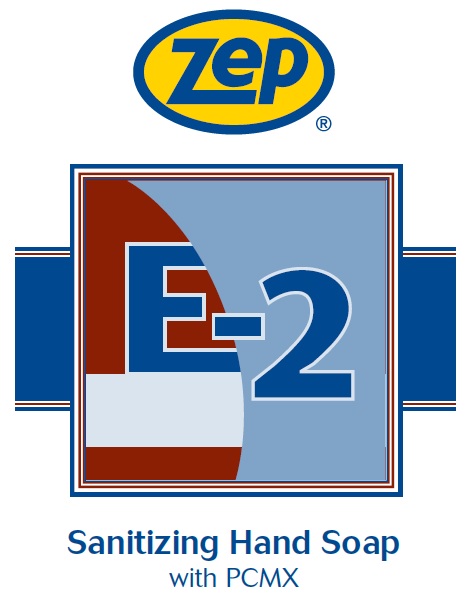 DRUG LABEL: Zep E-2 Hand Sanitizing Cleaner
NDC: 66949-125 | Form: LIQUID
Manufacturer: Zep Inc.
Category: otc | Type: HUMAN OTC DRUG LABEL
Date: 20251226

ACTIVE INGREDIENTS: CHLOROXYLENOL 3 g/100 mL
INACTIVE INGREDIENTS: WATER; SODIUM C14-16 OLEFIN SULFONATE; TRIETHYLENE GLYCOL; COCAMIDOPROPYL HYDROXYSULTAINE; HYDROXYETHYL CELLULOSE (2000 CPS AT 1%); PEG-75 LANOLIN; METHYLCHLOROISOTHIAZOLINONE; METHYLISOTHIAZOLINONE; ANHYDROUS CITRIC ACID

66949-125 / 0920 E-2 Hand Sanitizing Cleaner

Active ingredient

Chloroxylenol 3.0%

Purpose

Antiseptic Hand Wash

Uses

Hand washing to decrease bacteria on skin

Warnings

For external use only.

Do not use in or around the eyes.

When using this product

- If eye contact occurs, rinse promptly and thoroughly with water.
- Do not swallow.
- If swallowed, do not induce vomiting and if individual is conscious, give large quantities of water to drink and consult a physician immediately.
- Allergy alert: May cause skin reactions. Symptoms may include: skin reddening, blisters, rash
- If a skin reaction occurs, stop use and seek medical help right away

Stop use and ask a doctor if skin irritation or redness persists for more than 72 hours.

Keep out of reach of children and pets. Children must be supervised in use of this product.

Directions

- Wet hands with water.
- Place hands under dispenser and apply liquid soap.
- Massage soap into hands and wrists, emphasizing back of hands, knuckles and cuticles.
- Rinse hands thoroughly and dry.

Other information

- Store at room temperature.
- Do not freeze.
- Dispose in accordance with all applicable federal, state and local regulations.

Inactive ingredients

Water, Sodium C14-16 Olefin Sulfonate, Triethylene Glycol, Cocamidopropyl Hydroxysultaine, Hydroxyethyl Cellulose, PEG-75 Lanolin, Methylchloroisothiazolinone, Methylisothiazolinone, Citric Acid

Questions of comments?

Call 1-877-I-BUY_ZEP (1-877-428-9937)